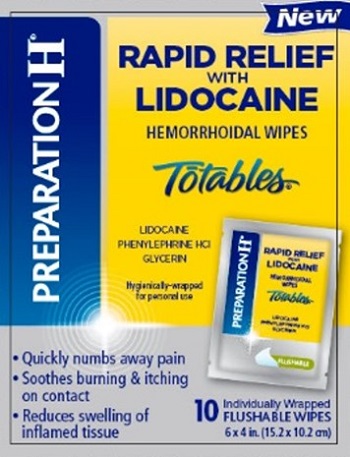 DRUG LABEL: Preparation H Rapid Relief
NDC: 0573-0554 | Form: CLOTH
Manufacturer: Haleon US Holdings LLC
Category: otc | Type: HUMAN OTC DRUG LABEL
Date: 20240301

ACTIVE INGREDIENTS: GLYCERIN 200 mg/1 1; LIDOCAINE 50 mg/1 1; PHENYLEPHRINE HYDROCHLORIDE 2.5 mg/1 1
INACTIVE INGREDIENTS: ALOE VERA LEAF; ANHYDROUS CITRIC ACID; BENZYL ALCOHOL; EDETATE DISODIUM; PROPYLENE GLYCOL; WATER; SODIUM BENZOATE

Drug Facts

ACTIVE INGREDIENT

PURPOSE

Active ingredients | Purposes
Glycerin 20% | Protectant
Lidocaine 5% | Local anesthetic
Phenylephrine HCl 0.25% | Vasoconstrictor

Uses

- for temporary relief of pain, soreness and burning
- helps relieve the local itching and discomfort associated with hemorrhoids
- temporarily reduces the swelling associated with irritated hemorrhoidal tissue
- temporarily provides a coating for relief of anorectal discomforts
- temporarily protects the inflamed, irritated anorectal surface to help make bowel movements less painful

Warnings

For external use only

Ask a doctor before use if you have

- heart disease
- high blood pressure
- thyroid disease
- diabetes
- difficulty in urination due to enlargement of the prostate gland

Ask a doctor or pharmacist before use if you arepresently taking a prescription drug for high blood pressure or depression.

When using this product

- wash hands after use. Avoid contact with eyes
- do not exceed the recommended daily dosage unless directed by a doctor
- do not put this product into the rectum by using fingers or any mechanical device or applicator

Stop use and ask a doctor if

- bleeding occurs
- condition worsens or does not improve within 7 days
- an allergic reaction develops
- the symptom being treated does not subside or if redness, irritation, swelling, pain, or other symptoms develop or increase

PREGNANCY OR BREAST FEEDING

If pregnant or breast-feeding,ask a health professional before use.

Keep out of reach of children.If swallowed, get medical help or contact a Poison Control Center right away.

Directions

- adults: when practical, cleanse the affected area with mild soap and warm water and rinse thoroughly. Gently dry by patting or blotting with a tissue or soft cloth before applying wipe.
- apply externally to affected area up to 4 times daily.
- unfold wipe and gently apply to the affected area by patting and then discard.
- children under 12 years of age: ask a doctor

Other information

- store at 20-25°C (68-77°F)
- for best results, flush only one at a time

Inactive ingredients

aloe barbadensis leaf juice, anhydrous citric acid, benzyl alcohol, edetate disodium, propylene glycol, purified water, sodium benzoate

Questions or comments?

Call weekdays 9 AM to 5 PM EST at 1-800-99PrepHor 1-800-997-7374

PRINCIPAL DISPLAY PANEL - 10 Wipe Pouch Carton

PREPARATION H®

New

RAPID RELIEF
WITH
LIDOCAINE

HEMORRHOIDAL WIPES

Totables®

LIDOCAINE
PHENYLEPHRINE HCl
GLYCERIN

Hygienically-wrapped
for personal use

- Quickly numbs away pain
- Soothes burning & itching
  on contact
- Reduces swelling of
  inflamed tissue

10
Individually Wrapped
FLUSHABLE WIPES

6 x 4 in. (15.2 x 10.2 cm)